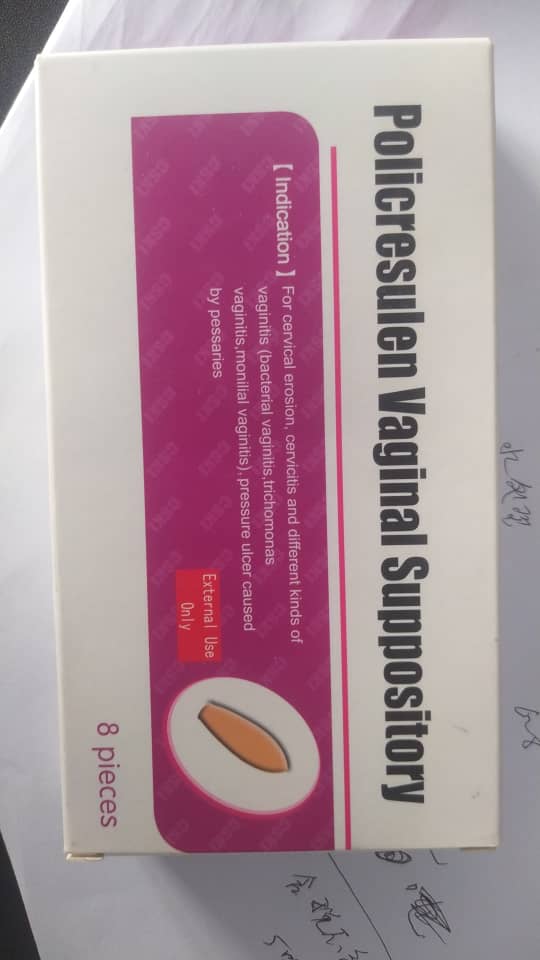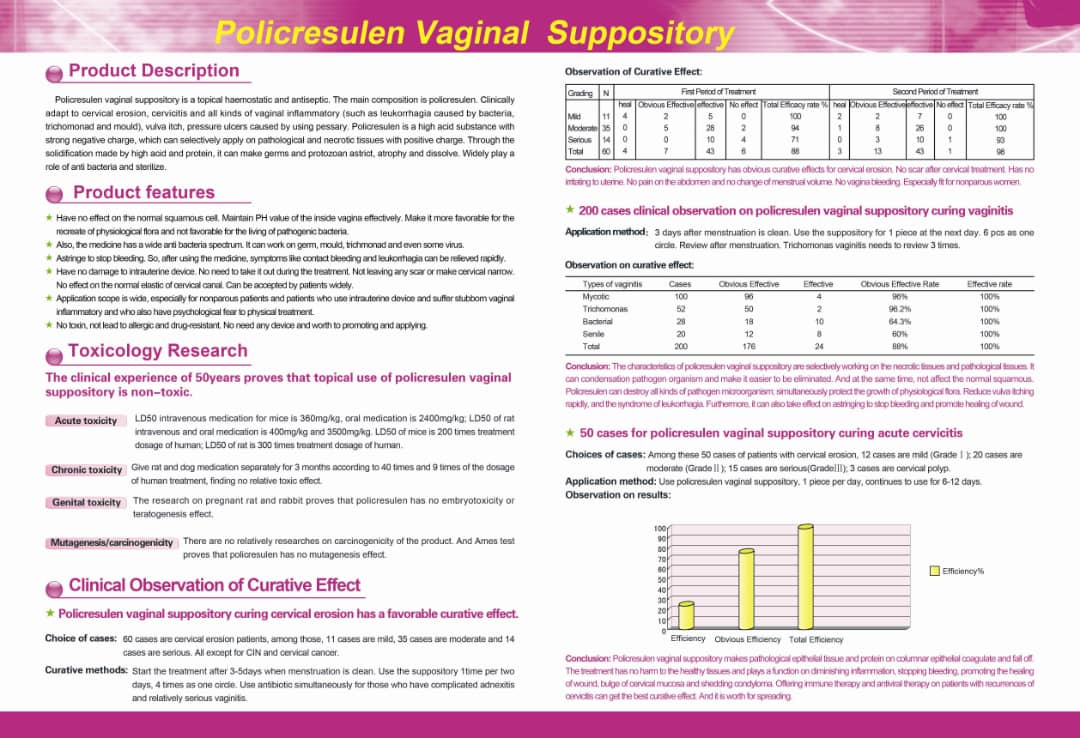 DRUG LABEL: Jujiafenhuangquan Yindaoshuan
NDC: 84149-0102 | Form: SUPPOSITORY
Manufacturer: Heilongjiang Tianlong Pharmaceutical Co Ltd
Category: otc | Type: HUMAN OTC DRUG LABEL
Date: 20240315

ACTIVE INGREDIENTS: POLICRESULEN 1 g/90 mg
INACTIVE INGREDIENTS: WATER

COMPONENTS

Instruction for Usage of Policresulen Vaginal Suppository

Please read the instruction carefully and use the product under the advice of doctor

Warning: during pregnancy, especially in the last three months of pregnancy, any treatment of the cervix should not be used, while the treatment of the vagina and its surrounding areas can only be used when absolutely necessary.

【Name】Policresulen Vaginal Suppository

Pin yin: Jujiafenhuangquan Yindaoshuan

【Ingredients】The main component of this product is Policresulen. Its chemical name is: m-cresol sulfonic acid and formaldehyde polymer.

【Character】This product is light red to light red brown suppository.

【Indication】It is used in the treatment of local inflammation or infection and tissue damage of vagina and cervix (eg, discharge due to bacterial, trichomonal and fungal infections, pressure sores from pessaries), condylomata acuminate, protuberance of cervical mucosa (cervical ectopia). For cervical erosion, cervicitis and different kinds of vaginitis.(Bacterial Vaginitis,Trichomonas Vaginitis,monilial vaginitis)pressure ulcer caused by Pessaries.

【Specification】8piece/box

【Usage and Dosage】 Vaginal administration, put the product into the deep part of the vagina, once every 2 days. If the affected part is burned with the Policresulen concentrated solution, a suppository should put in every other day between the two burns. For the convenience of use, the patient had better take the supine position, first wet the suppository with water, and then insert it into the deep part of vagina. Usually, it is better to use medicine before going to bed at night. Use with sanitary napkin together, to prevent pollution of clothes and bedding.

【Adverse Reactions】 Occasional local irritation will be occurred after treatment (such as burning or pain) usually can be tolerated and will soon disappear.

【Contraindications】 During pregnancy, especially in the last three months of pregnancy, any treatment of the cervix should not be used, while the treatment of the vagina and its surrounding areas can only be used when absolutely necessary.

【Precaution】

1. External use only, should not be taken orally.

2. This product should avoid contact with eyes.

3. This product will accelerate and enhance the repair process. If the necrotic tissue falls off from the focus, sometimes even a large sheet falls off. Do not panic.

4. Stop treatment during menstruation. Avoid sexual life during treatment. Do not use irritating soap to clean the affected area.

5. Cotton fabric and leather shall be washed with water immediately before the preparation is dry, when the solution contacting with them.

6. Spots on the vaginal suppository are the natural phenomena produced by its matrix, which do not affect the use and efficacy of the drug, nor affect its tolerance.

【Medication for pregnant women and lactating women】 During pregnancy, especially in the third trimester, any cervical treatment should be avoided, and the Policresulen suppository is no exception. At this time, the potential harm of the drug to the mother and baby should be fully considered. Although the animal test shows that the drug has no teratogenic effect, the results of the human test have not been obtained. It is unclear whether the milk of lactating women will contain the active ingredient of this medicine.

【Children Medication】The safety and efficacy of children patients have not been studied.

【Geriatric Medication】The safety and efficacy of elderly patients have not been studied.

【Drug Interactions】Policresulen can only be used locally. Since the interaction with other drugs cannot be ruled out, it is avoided to use more than two drugs at the same place at the same time.

【Pharmacology and Toxicology】

Pharmacological Action

The mechanism of action of policresulen is to kill bacteria, haze bacteria and trichomonad by strong acid and protein coagulation. Selectively cause necrosis or pathological tissue and columnar epithelial protein denaturation. It causes vasoconstriction and plasma protein coagulation to stop bleeding.

Policresulen has a wide range of antibacterial activities, including common gram-positive bacteria, Gram-negative bacteria, fungi and some viruses, of which Gardnerella vaginatis, anaerobic trichomonad and Candida are particularly sensitive. But Doderlein bacterial flora was not affected. At present, the drug has not been reported to cause drug resistance.

Policresulen can selectively coagulate necrotic or diseased tissues and promote tissue regeneration and epithelial re covering. Healthy squamous epithelium is unaffected, while the cytoplasm and nucleus of columnar epithelium may swell after contact with the drug, and then shrink in a few seconds. Local application of policresulen does not produce toxicity.

Toxicity Studying

More than 50 years of clinical experience has proved that the local use of policresulen is non-toxic.

Acute toxicity: The LD50 of mice was 360mg/kg after intravenous administration and 2400mg/kg after oral administration. The LD50 of rats was 400mg/kg intravenously and 3500mg/kg orally. The LD50 of mice is 200 times of the therapeutic dose of human beings, and the LD50 of rats is 300 times of the therapeutic dose of human beings.

Chronic toxicity: Rats and dogs were given 40 times and 9 times of the human treatment dose for 3 months, no related toxic effect was found.

The skin tolerance test of policresulen was carried out on the back of hair removing rats. In the first 10 days of the 14 day observation, the application of different concentrations of policresulen (4%, 11% and 36%) only caused temporary skin redness, which lasted until the third application at most.

Reproductive toxicity: The study on pregnant rats and rabbits shows that there was no embryotoxicity or teratogenicity effect on animals. teratogenicity

Mutagenicity/carcinogenicity: there is no relevant study on the carcinogenesis of this product. Ames test proves that policresulen has no mutagenic effect there is no relevant research on the carcinogenesis of this product. Ames test proves that policresulen has no mutagenicity effects. Although there is no research report on carcinogenesis of this product, no mutagenic or carcinogenic effect has been found in clinical application for many years.

【Pharmacokinetic】 Data are still lacking

【Shelf Life】 36 months

【Storage】Shading, airtight, stored below 25 ℃

【Package】 Medical polyethylene PVC composite packaging. 8 capsules per box. 8 medical plastic fingertips.

【Validity Period】 36 months

【Executive Standard】National Food and Drug Administration Standard YBH02122009

【Approval No. 】National Drug Approval No. H20093211

【Production Enterprise】

Name: Heilongjiang Tianlong Pharmaceutical Co., Ltd.

Address: NO.158, Jiuzhou Road, Industry Park, Harbin Science and Technology Innovation City, Harbin, China

Post code: 150020

Tel: 400-657-8838

Fax No.: 0451-87032629

Website: WW. Hutl. Com

DOSAGE AND ADMINISTRATION

【Indication】It is used in the treatment of local inflammation or infection and tissue damage of vagina and cervix (eg, discharge due to bacterial, trichomonal and fungal infections, pressure sores from pessaries), condylomata acuminate, protuberance of cervical mucosa (cervical ectopia). For cervical erosion, cervicitis and different kinds of vaginitis.(Bacterial Vaginitis,Trichomonas Vaginitis,monilial vaginitis)pressure ulcer caused by Pessaries.

【Specification】8piece/box

【Usage and Dosage】 Vaginal administration, put the product into the deep part of the vagina, once every 2 days. If the affected part is burned with the Policresulen concentrated solution, a suppository should put in every other day between the two burns. For the convenience of use, the patient had better take the supine position, first wet the suppository with water, and then insert it into the deep part of vagina. Usually, it is better to use medicine before going to bed at night. Use with sanitary napkin together, to prevent pollution of clothes and bedding.

INACTIVE INGREDIENT

【Ingredients】The main component of this product is Policresulen. Its chemical name is: m-cresol sulfonic acid and formaldehyde polymer.

【Character】This product is light red to light red brown suppository.

INDICATIONS AND USAGE

【Precaution】

1. External use only, should not be taken orally.

2. This product should avoid contact with eyes.

3. This product will accelerate and enhance the repair process. If the necrotic tissue falls off from the focus, sometimes even a large sheet falls off. Do not panic.

4. Stop treatment during menstruation. Avoid sexual life during treatment. Do not use irritating soap to clean the affected area.

5. Cotton fabric and leather shall be washed with water immediately before the preparation is dry, when the solution contacting with them.

6. Spots on the vaginal suppository are the natural phenomena produced by its matrix, which do not affect the use and efficacy of the drug, nor affect its tolerance.

【Medication for pregnant women and lactating women】 During pregnancy, especially in the third trimester, any cervical treatment should be avoided, and the Policresulen suppository is no exception. At this time, the potential harm of the drug to the mother and baby should be fully considered. Although the animal test shows that the drug has no teratogenic effect, the results of the human test have not been obtained. It is unclear whether the milk of lactating women will contain the active ingredient of this medicine.

【Children Medication】The safety and efficacy of children patients have not been studied.

【Geriatric Medication】The safety and efficacy of elderly patients have not been studied.

【Drug Interactions】Policresulen can only be used locally. Since the interaction with other drugs cannot be ruled out, it is avoided to use more than two drugs at the same place at the same time.

Medicine Keep out of reach of children.

PURPOSE

【Pharmacology and Toxicology】

Pharmacological Action

The mechanism of action of policresulen is to kill bacteria, haze bacteria and trichomonad by strong acid and protein coagulation. Selectively cause necrosis or pathological tissue and columnar epithelial protein denaturation. It causes vasoconstriction and plasma protein coagulation to stop bleeding.

Policresulen has a wide range of antibacterial activities, including common gram-positive bacteria, Gram-negative bacteria, fungi and some viruses, of which Gardnerella vaginatis, anaerobic trichomonad and Candida are particularly sensitive. But Doderlein bacterial flora was not affected. At present, the drug has not been reported to cause drug resistance.

Policresulen can selectively coagulate necrotic or diseased tissues and promote tissue regeneration and epithelial re covering. Healthy squamous epithelium is unaffected, while the cytoplasm and nucleus of columnar epithelium may swell after contact with the drug, and then shrink in a few seconds. Local application of policresulen does not produce toxicity.

Toxicity Studying

More than 50 years of clinical experience has proved that the local use of policresulen is non-toxic.

Acute toxicity: The LD50 of mice was 360mg/kg after intravenous administration and 2400mg/kg after oral administration. The LD50 of rats was 400mg/kg intravenously and 3500mg/kg orally. The LD50 of mice is 200 times of the therapeutic dose of human beings, and the LD50 of rats is 300 times of the therapeutic dose of human beings.

Chronic toxicity: Rats and dogs were given 40 times and 9 times of the human treatment dose for 3 months, no related toxic effect was found.

The skin tolerance test of policresulen was carried out on the back of hair removing rats. In the first 10 days of the 14 day observation, the application of different concentrations of policresulen (4%, 11% and 36%) only caused temporary skin redness, which lasted until the third application at most.

Reproductive toxicity: The study on pregnant rats and rabbits shows that there was no embryotoxicity or teratogenicity effect on animals. teratogenicity

Mutagenicity/carcinogenicity: there is no relevant study on the carcinogenesis of this product. Ames test proves that policresulen has no mutagenic effect there is no relevant research on the carcinogenesis of this product. Ames test proves that policresulen has no mutagenicity effects. Although there is no research report on carcinogenesis of this product, no mutagenic or carcinogenic effect has been found in clinical application for many years.

WARNINGS

Please read the instruction carefully and use the product under the advice of doctor

Warning: during pregnancy, especially in the last three months of pregnancy, any treatment of the cervix should not be used, while the treatment of the vagina and its surrounding areas can only be used when absolutely necessary.

ACTIVE INGREDIENT

【Ingredients】The main component of this product is Policresulen. Its chemical name is: m-cresol sulfonic acid and formaldehyde polymer.

Content of Labeling

Instruction for Usage of Policresulen Vaginal Suppository

Please read the instruction carefully and use the product under the advice of doctor

Warning: during pregnancy, especially in the last three months of pregnancy, any treatment of the cervix should not be used, while the treatment of the vagina and its surrounding areas can only be used when absolutely necessary.